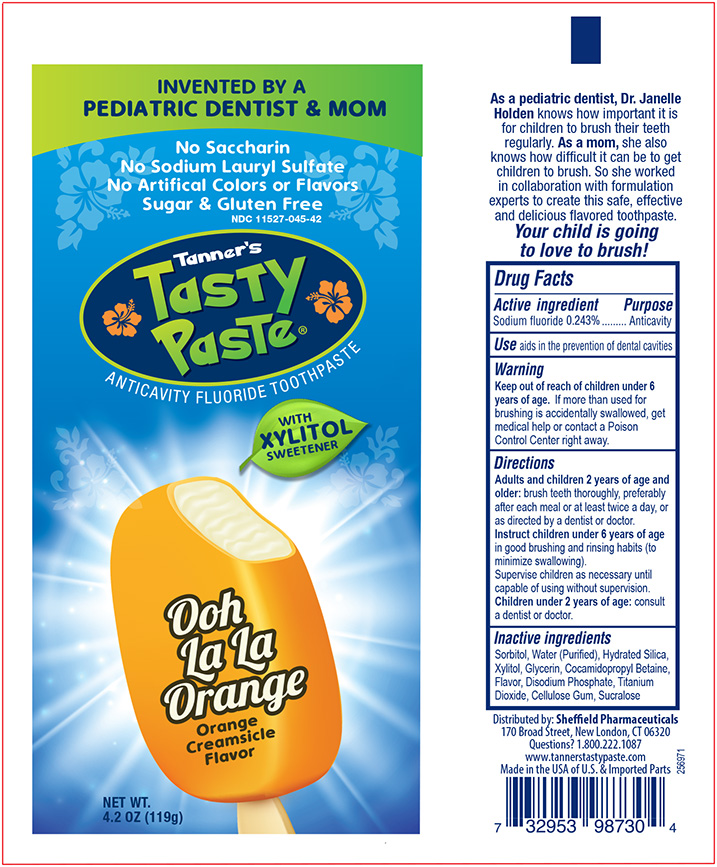 DRUG LABEL: Tanners Tasty Ooh La La Orange
NDC: 11527-045 | Form: PASTE, DENTIFRICE
Manufacturer: Sheffield Pharmaceuticals LLC
Category: otc | Type: HUMAN OTC DRUG LABEL
Date: 20231024

ACTIVE INGREDIENTS: SODIUM FLUORIDE 2.43 mg/1 g
INACTIVE INGREDIENTS: SORBITOL; WATER; HYDRATED SILICA; XYLITOL; GLYCERIN; COCAMIDOPROPYL BETAINE; CARBOXYMETHYLCELLULOSE; TITANIUM DIOXIDE; SODIUM PHOSPHATE DIBASIC DIHYDRATE; SUCRALOSE

Tanners Tasty Paste Ooh La La Orange

Active Ingredient:

Sodium fluoride - 0.243%

PURPOSE

Anticavity toothpaste

Uses:

- Aids in the prevention of dental decay

Warnings:

- If more than used for brushing is accidentally swallowed, get medical help or contact a Poison Control Center right away.

KEEP OUT OF REACH OF CHILDREN

Keep out of the reach of children under 6 years of age.

Directions:

- Adults and Children 2 years of age and older: Brush teeth thoroughly, preferably after each meal or at least twice a day, or as directed by a dentist or doctor.
- Instruct children 6 years of age in good brushing and rinsing habits (to minimize swallowing), and and only use a pea size amount.
- Supervise children as necessary until capable of using without supervision.
- Chlidren under 2 years of age: Conmsult a dentist or doctor.

Inactive ingredients:

Inactive Ingredients: Sorbitol, Purified Water, Hydrated Silica, Xylitol, Glycerin, Cocamidopropyl Betaine, Flavor, Cellulose Gum, Titanium Dioxide, Disodium Phosphate, Sucralose

Principal Panel 4.2 OZ Tube

Tanner Tasty Paste NDC 11527-045-42

0.243% Sodium Fluoride Toothpaste

Ooh La La Orange

NET WT. 4.2 oz (119g)